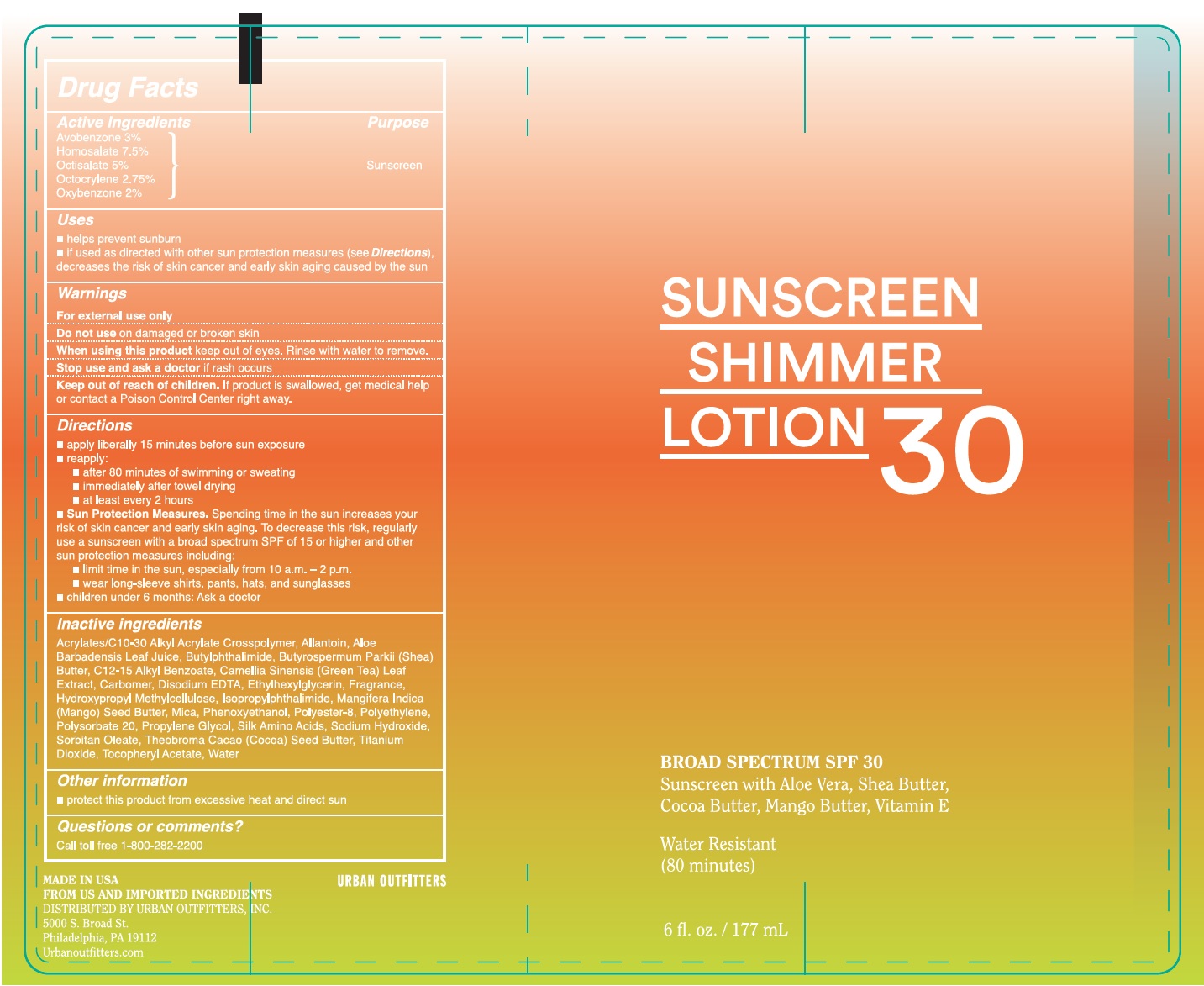 DRUG LABEL: Urban Outfitters
NDC: 58443-0259 | Form: LOTION
Manufacturer: Prime Enterprises Inc.
Category: otc | Type: HUMAN OTC DRUG LABEL
Date: 20200117

ACTIVE INGREDIENTS: OXYBENZONE 20.2 mg/1 mL; AVOBENZONE 30.3 mg/1 mL; OCTISALATE 50.5 mg/1 mL; OCTOCRYLENE 27.78 mg/1 mL; HOMOSALATE 75.75 mg/1 mL
INACTIVE INGREDIENTS: AMINO ACIDS, SILK; GREEN TEA LEAF; CARBOMER HOMOPOLYMER TYPE C; EDETATE DISODIUM; ETHYLHEXYLGLYCERIN; HYPROMELLOSES; MANGIFERA INDICA SEED BUTTER; POLYESTER-8 (1400 MW, CYANODIPHENYLPROPENOYL CAPPED); HIGH DENSITY POLYETHYLENE; POLYSORBATE 20; ALLANTOIN; N-BUTYLPHTHALIMIDE; SHEA BUTTER; COCOA BUTTER; CARBOMER 1342; ALOE VERA LEAF; ALKYL (C12-15) BENZOATE; ISOPROPYLPHTHALIMIDE; MICA; PHENOXYETHANOL; PROPYLENE GLYCOL; SODIUM HYDROXIDE; SORBITAN MONOOLEATE; TITANIUM DIOXIDE; .ALPHA.-TOCOPHEROL ACETATE; WATER

Urban Outfitters Sunscreen Shimmer Lotion 30 Broad Spectrum SPF 30

Active Ingredients

Avobenzone 3%

Homosalate 7.5%

Octisalate 5%

Octocrylene 2.75%

Oxybenzone 2%

Purpose

Sunscreen

Uses

• helps prevent sunburn

• if used as directed with other sun protection measures (see Directions), decreases the risk of skin cancer and early skin aging caused by the sun.

Warnings

For external use only

Do not use on damaged or broken skin

When using this product keep out of eyes. Rinse with water to remove.

Stop use and ask a doctor if rash occurs

Keep out of reach of children. If product is swallowed, get medical help or contact a Poison Control Center right away.

Directions

- apply liberally 15 minutes before sun exposure
- reapply:
- after 80 minutes of swimming or sweating
- immediately after towel drying
- at least every 2 hours
- Sun Protection Measures. Spending time in the sun increases your risk of skin cancer and early skin aging. To decrease this risk, regularly use a sunscreen with broad spectrum SPF of 15 or higher and other sun protection measures including:
- limit time in the sun, especially from 10 a.m. – 2 p.m.
- wear long-sleeve shirts, pants, hats, and sunglasses
- children under 6 months: Ask a doctor

Inactive ingredients

Acrylates/C10-30 Alkyl Acrylate Crosspolymer, Allantoin, Aloe Barbadensis Leaf Juice, Butylphthalimide, Butyrospermum Parkii (Shea) Butter, C12-15 Alkyl Benzoate, Camellia Sinensis (Green Tea) Leaf Extract, Carbomer, Disodium EDTA, Ethylhexylglycerin, Fragrance, Hydroxypropyl Methylcellulose, Isopropylphthalimide ,Mangifera Indica (Mango) Seed Butter, Mica, Phenoxyethanol, Polyester-8, Polyethylene, Polysorbate 20, Propylene Glycol, Silk Amino Acids, Sodium Hydroxide, Sorbitan Oleate, Theobroma Cacao (Cocoa) Seed Butter, Titanium Dioxide, Tocopheryl Acetate, Water

Other information

- Protect this product from excessive heat and direct sun

Questions or comments?

Call toll free 1-800-282-2200